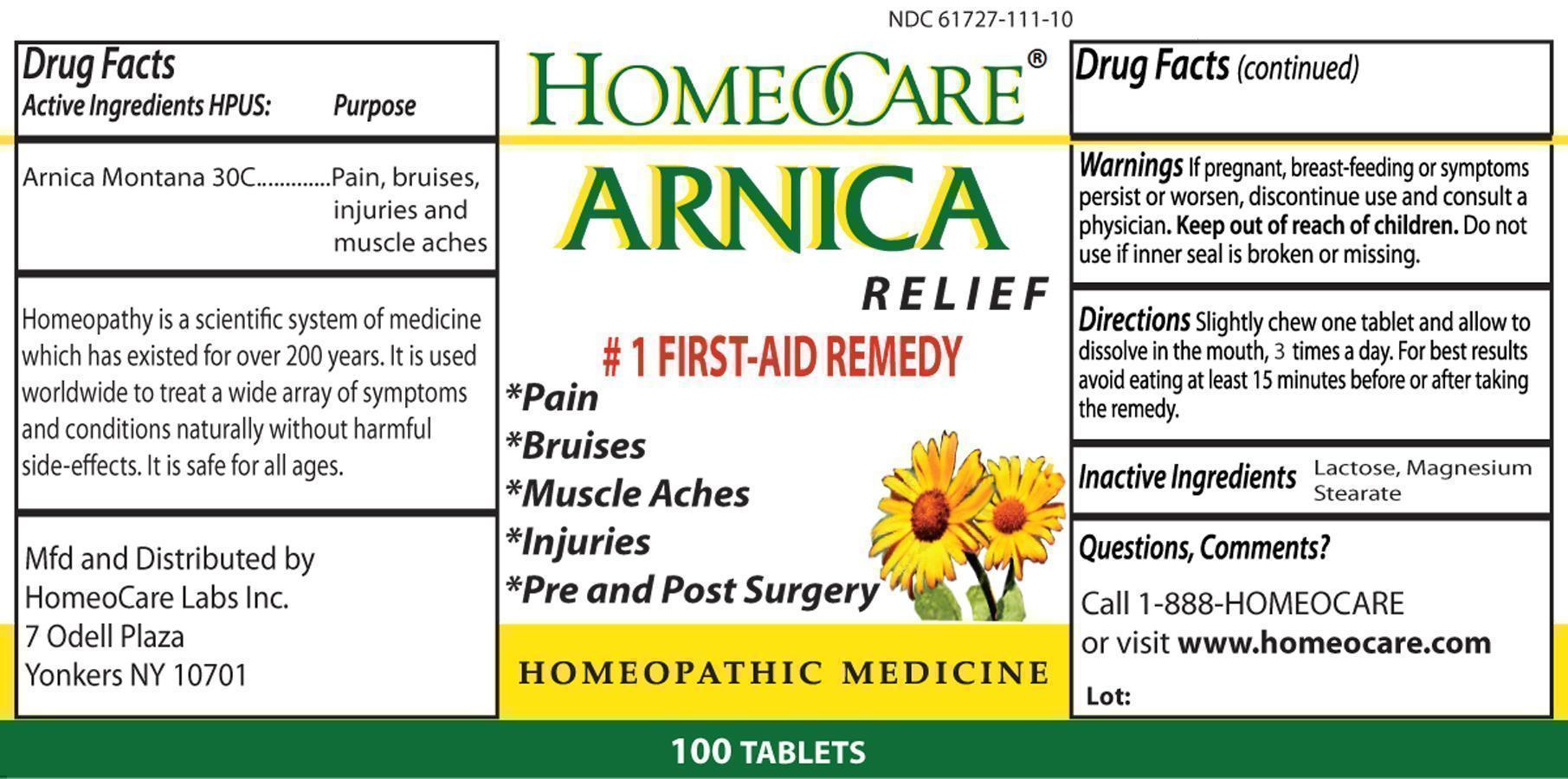 DRUG LABEL: Arnica Relief
NDC: 61727-111 | Form: TABLET
Manufacturer: Homeocare Laboratories
Category: homeopathic | Type: HUMAN OTC DRUG LABEL
Date: 20181221

ACTIVE INGREDIENTS: ARNICA MONTANA 30 [hp_C]/1 1
INACTIVE INGREDIENTS: LACTOSE; MAGNESIUM STEARATE

Arnica Relief Tablets

Active Ingredients:

Arnica Montana 30C

Inactive Ingredients:

Lactose, Magnesium Stearate

Purpose:

For relief of pain, bruises, muscle aches, injuries, and pre and post surgery.

Keep out of reach of children.

Indications & Usage:

Slightly chew one tablet and allow to dissolve in the mouth, 3 times a day. For best results avoid eating at least 15 minutes before or after taking the remedy.

Warnings:

If pregnant, breast-feeding or symptoms persist or worsen, discontinue use and consult a physician. Keep out of reach of children. Do not use if inner seal is broken or missing.

Dosage & Administration:

Slightly chew one tablet and allow to dissolve in the mouth, 3 times a day. For best results avoid eating at least 15 minutes before or after taking the remedy.